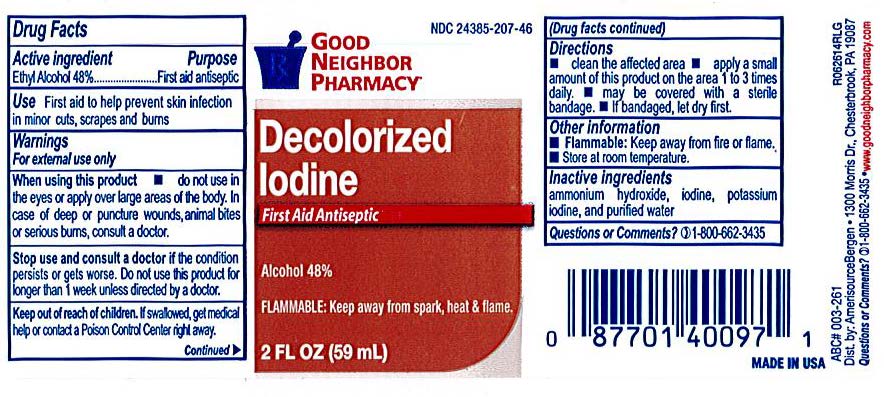 DRUG LABEL: Isopropyl Alcohol
NDC: 24385-207 | Form: LIQUID
Manufacturer: Amerisource Bergen
Category: otc | Type: HUMAN OTC DRUG LABEL
Date: 20231214

ACTIVE INGREDIENTS: ISOPROPYL ALCOHOL 70 mL/100 mL
INACTIVE INGREDIENTS: AMMONIA; IODINE; POTASSIUM IODIDE; WATER

GNP Decolorized Iodine

Drug Facts

Active Ingredients

Ethyl Alcohol 48%

Purpose

First Aid Antiseptic

Uses

First aid to help prevent infection in minor cuts, scrapes and burns.

Warnings

For external use only.

Ask a doctor before use if you have

deep or puncture wounds, animal bites, serious burns.

Stop use and ask a doctor if:

The condition persists or gets worse, or if using this product for longer than 1 week.

When using this product:

Do not use in the eyes. If contact occurs, flush with large amounts of water while lifting upper and lower lids. Do not apply over large areas of the body.

Keep out of the reach of children.

If swallowed, get medical help or contact a Poison Control Center right away..

Directions

Clean the affected area. Aply a small amount to the affected area 1 to 3 times daily. May be covered with a sterile bandage. If bandaged, let it dry first.

Inactive Ingredient:

Ammoniuim Hydroxide, iodine, potasssium iodide, purified water.

Other Information:

Flammable. Keep away form fire or flame.

Store at room temperature.